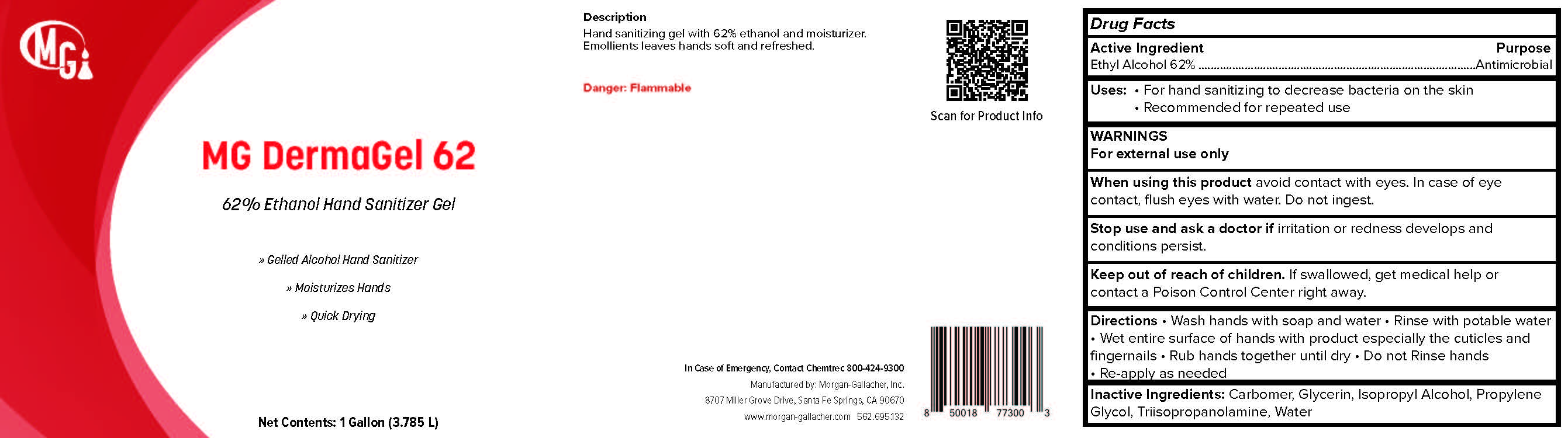 DRUG LABEL: MG DermaGel 62
NDC: 50241-326 | Form: LIQUID
Manufacturer: Morgan Gallacher Inc. DBA Custom Chemical Formulators Inc.
Category: otc | Type: HUMAN OTC DRUG LABEL
Date: 20251229

ACTIVE INGREDIENTS: ALCOHOL 0.62 L/1 L
INACTIVE INGREDIENTS: WATER; GLYCERIN; PROPYLENE GLYCOL; TRIISOPROPANOLAMINE

MG DermaGel 62

Active Ingredient

Ethyl Alcohol....62%

Purpose

Antimicrobial

Uses

- For hand sanitizing to decrease bacteria on the skin
- Recommended for repeated use

Warnings

- For external use only.
- Flammable keep away from fire or flame

When using this product

- Avoid contact with eyes. In case of eye contract, flush eyes with water.

Stop use and ask doctor if

- irritation or redness develops, if condition persists for more than 72 hours.

Keep out of reach of children

If swallowed, get medical help or contact a Poison Conrol Center right away

Directions

- Place a small amount of MG Dermagel 62 in your palm to throughly cover your hands.
- Rub hands together briskly until dry.
- Keep out of reach of children. For children under 6, use only under adult supervison. Not recommended for infants.

Inactive Ingredients

- Water
- Isopropyl Alcohol
- Glycerin
- Propylene Glycol
- Carbomer
- Triisopropanolamine